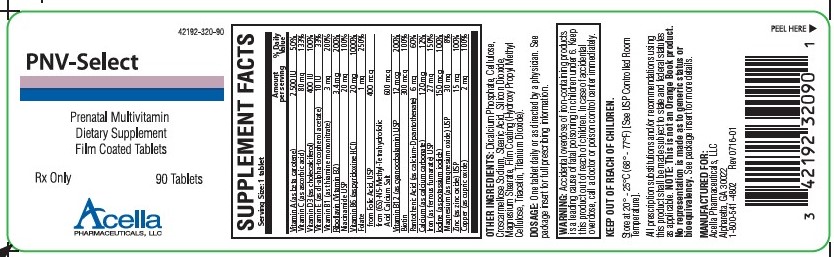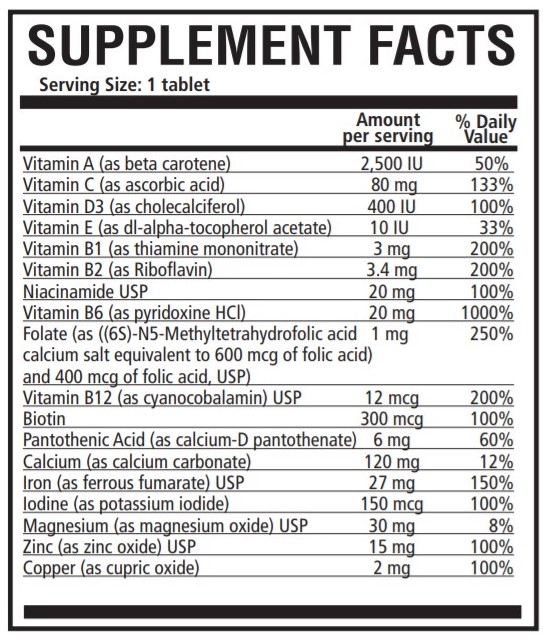 DRUG LABEL: PNV-Select
NDC: 42192-320 | Form: TABLET, FILM COATED
Manufacturer: Acella Pharmaceuticals, LLC
Category: prescription | Type: HUMAN PRESCRIPTION DRUG LABEL
Date: 20240116

ACTIVE INGREDIENTS: VITAMIN A ACETATE 2500 [iU]/1 1; ASCORBIC ACID 80 mg/1 1; CHOLECALCIFEROL 400 [iU]/1 1; .ALPHA.-TOCOPHEROL ACETATE, DL- 10 [iU]/1 1; THIAMINE MONONITRATE 3 mg/1 1; RIBOFLAVIN 3.4 mg/1 1; NIACINAMIDE 20 mg/1 1; PYRIDOXINE HYDROCHLORIDE 20 mg/1 1; FOLIC ACID 1 mg/1 1; CYANOCOBALAMIN 12 ug/1 1; BIOTIN 300 ug/1 1; CALCIUM PANTOTHENATE 6 mg/1 1; CALCIUM CARBONATE 120 mg/1 1; FERROUS FUMARATE 27 mg/1 1; POTASSIUM IODIDE 150 ug/1 1; MAGNESIUM OXIDE 30 ug/1 1; ZINC OXIDE 15 ug/1 1; CUPRIC OXIDE 2 mg/1 1
INACTIVE INGREDIENTS: CALCIUM PHOSPHATE, DIBASIC, ANHYDROUS; CELLULOSE, MICROCRYSTALLINE; STEARIC ACID; CROSCARMELLOSE SODIUM; SILICON DIOXIDE; MAGNESIUM STEARATE; TITANIUM DIOXIDE

PNV-Select

Rx Only

DESCRIPTION

DESCRIPTION: PNV-Select is a prescription prenatal dietary supplement tablet that contains multivitamins and minerals, which are delivered in the form of a white, oval, oil-and water-soluble, film-coated tablet debossed with “320” on one side.

OTHER INGREDIENTS: Dicalcium Phosphate, Cellulose, Croscarmellose Sodium, Stearic Acid, Silicon Dioxide, Magnesium Stearate, Film Coating (Hydroxy Propyl Methyl Cellulose, Triacetin, Titanium Dioxide).

INDICATIONS AND USAGE

INDICATIONS: PNV-Select is a multivitamin/multimineral nutritional supplement indicated for use in the dietary management of patients with nutritional deficiencies or are in need of nutritional supplementation.

CONTRAINDICATIONS

CONTRAINDICATIONS: This product is contraindicated in patients with a known hypersensitivity to any of the ingredients.

BOXED WARNING

WARNING: Accidental overdose of iron-containing products is a leading cause of fatal poisoning in children under 6. Keep this product out of reach of children. In case of accidental overdose, call a doctor or poison control center immediately.

KEEP THIS AND ALL MEDICATIONS OUT OF THE REACH OF CHILDREN.

PRECAUTIONS

PRECAUTIONS: Folic acid alone is improper therapy in the treatment of pernicious anemia and other megaloblastic anemias where Vitamin B12 is deficient. Folic acid in doses above 1.0 mg daily may obscure pernicious anemia in that hematologic remission can occur while neurological manifestations progress.

ADVERSE REACTIONS

ADVERSE REACTIONS: Allergic sensitization has been reported following both oral and parenteral administration of folic acid.

DOSAGE AND ADMINISTRATION: One tablet daily or as directed by a physician.

HOW SUPPLIED

HOW SUPPLIED: PNV-Select is supplied in child-resistant bottles of 90 tablets (42192-320-90). The listed product is not a National Drug Code, but has merely been formatted to comply with standard industry practice for pharmacy and insurance computer systems.

STORAGE AND HANDLING

Store at 20°-25°C (68°-77°F); excursions permitted to 15°-30°C (59°-86°F). [See USP Controlled Room Temperature.]

All prescription substitutions and/or recommendations using this product shall be made subject to state and federal statutes as applicable. NOTE: This is not an Orange Book product and has not been subjected to FDA therapeutic equivalency or other equivalency testing. No representation is made as to generic status or bioequivalency. Each person recommending a prescription substitution using this product shall make such recommendations based on each such person’s professional opinion and knowledge, upon evaluating the dietary ingredients, other ingredients and information provided herein.

THESE STATEMENTS HAVE NOT BEEN EVALUATED BY THE FOOD AND DRUG ADMINISTRATION. THIS PRODUCT IS NOT INTENDED TO DIAGNOSE, TREAT, CURE OR PREVENT ANY DISEASE.

MANUFACTURED FOR:

Acella Pharmaceuticals, LLC

Alpharetta, GA 30005

1-800-541-4802

Rev 0719-03

PRINCIPAL DISPLAY PANEL - Film Coated Tablets

NDC 42192-320-90

PNV-Select

Prenatal Multivitamin

Dietary Supplement

Film Coated Tablets

Rx Only 90 Tablets

Acella
PHARMACEUTICALS, LLC